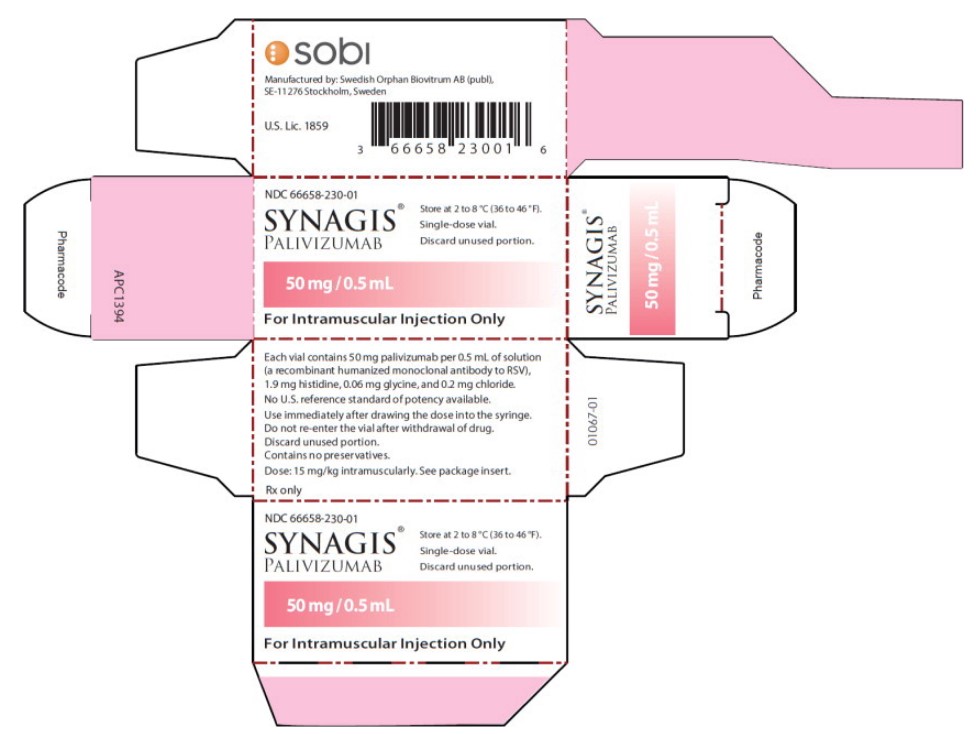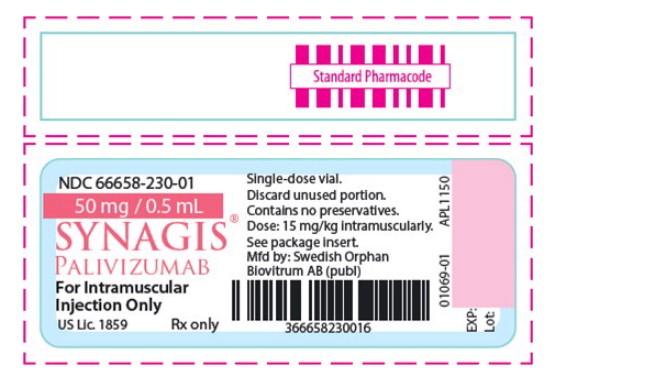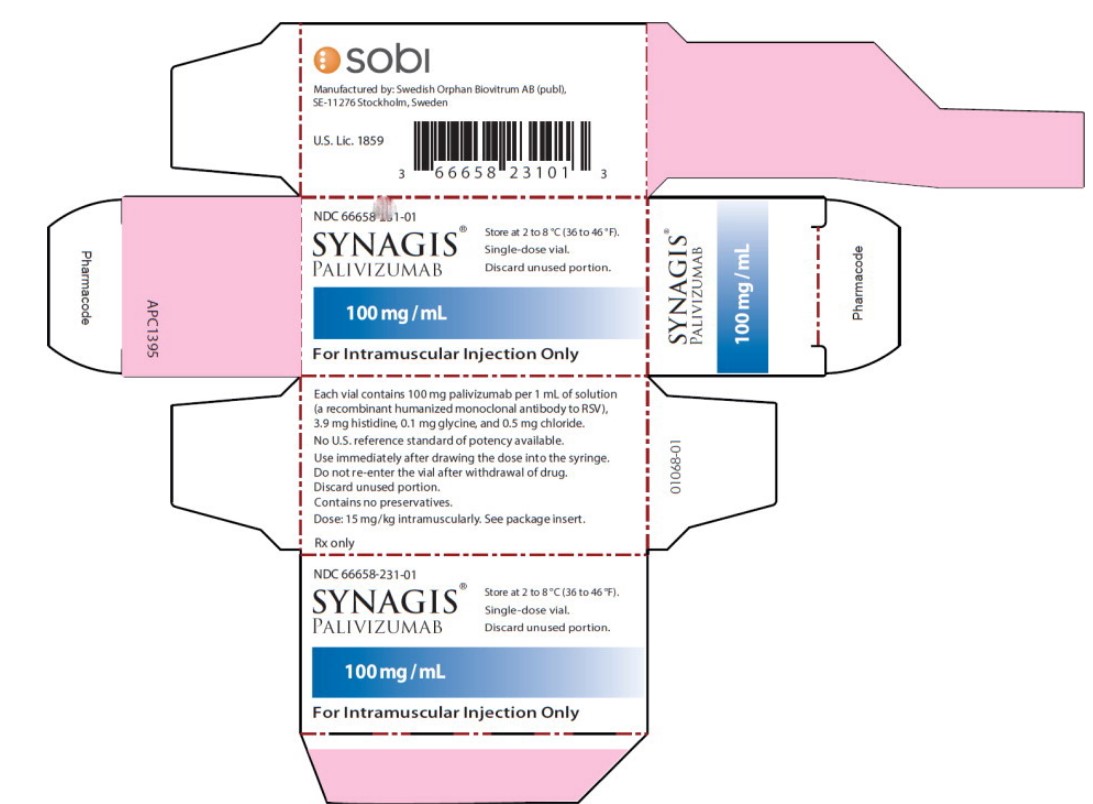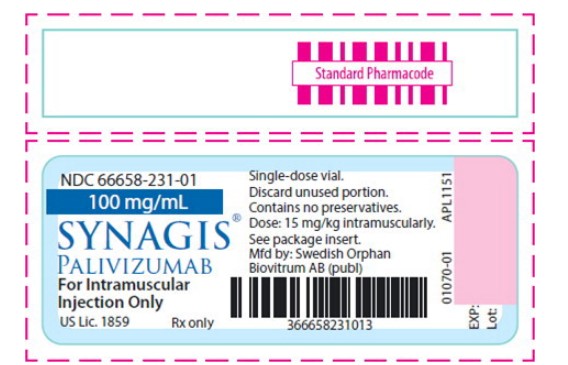 DRUG LABEL: Synagis

NDC: 66658-231 | Form: INJECTION, SOLUTION
Manufacturer: Swedish Orphan Biovitrum AB (publ)
Category: prescription | Type: HUMAN PRESCRIPTION DRUG LABEL
Date: 20260121

ACTIVE INGREDIENTS: PALIVIZUMAB
 100 mg/1 mL
INACTIVE INGREDIENTS: CHLORIDE ION 0.5 mg/1 mL; GLYCINE 0.1 mg/1 mL; HISTIDINE 3.9 mg/1 mL

HIGHLIGHTS OF PRESCRIBING INFORMATION

These highlights do not include all the information needed to use SYNAGIS safely and effectively. See full prescribing information for SYNAGIS.
SYNAGIS®(palivizumab) injection, for intramuscular use
Initial U.S. Approval: 1998

1 INDICATIONS AND USAGE

Synagis is a respiratory syncytial virus (RSV) F protein inhibitor monoclonal antibody indicated for the prevention of serious lower respiratory tract disease caused by respiratory syncytial virus (RSV) in pediatric patients:

- with a history of premature birth (less than or equal to 35 weeks gestational age) and who are 6 months of age or younger at the beginning of RSV season,
- with bronchopulmonary dysplasia (BPD) that required medical treatment within the previous 6 months and who are 24 months of age or younger at the beginning of RSV season,
- with hemodynamically significant congenital heart disease (CHD) and who are 24 months of age or younger at the beginning of RSV season.

Limitations of Use:The safety and efficacy of Synagis have not been established for treatment of RSV disease. (1)

2 DOSAGE AND ADMINISTRATION

15 mg per kg of body weight, administered intramuscularly prior to commencement of the RSV season and remaining doses administered monthly throughout the RSV season. (2.1)

Children undergoing cardio-pulmonary bypass should receive an additional dose of Synagis as soon as possible after the cardio-pulmonary bypass procedure (even if sooner than a month from the previous dose). Thereafter, doses should be administered monthly as scheduled. (2.1, 12.3)

3 DOSAGE FORMS AND STRENGTHS

Single-dose liquid solution vials: 50 mg per 0.5 mL and 100 mg per 1 mL. (3)

4 CONTRAINDICATIONS

Previous significant hypersensitivity reaction to Synagis. (4)

5 WARNINGS AND PRECAUTIONS

- Anaphylaxis and anaphylactic shock (including fatal cases), and other severe acute hypersensitivity reactions have been reported. Permanently discontinue Synagis and administer appropriate medications if such reactions occur. (5.1)
- As with any intramuscular injection, Synagis should be given with caution to children with thrombocytopenia or any coagulation disorder. (5.2)
- Palivizumab may interfere with immunological-based RSV diagnostic tests such as some antigen detection-based assays. (5.3, 12.4)

6 ADVERSE REACTIONS

Adverse reactions occurring greater than or equal to 10% and at least 1% more frequently than placebo are fever and rash. (6.1)

To report SUSPECTED ADVERSE REACTIONS, contact 1-866-773-5274 or FDA at 1-800-FDA-1088 orwww.fda.gov/medwatch.

8 USE IN SPECIFIC POPULATIONS

Safety and effectiveness in children older than 24 months of age at the start of dosing have not been established. (8.4)

FULL PRESCRIBING INFORMATION

1 INDICATIONS AND USAGE

Synagis is indicated for the prevention of serious lower respiratory tract disease caused by respiratory syncytial virus (RSV) in pediatric patients:

- with a history of premature birth (less than or equal to 35 weeks gestational age) and who are 6 months of age or younger at the beginning of RSV season,
- with bronchopulmonary dysplasia (BPD) that required medical treatment within the previous 6 months and who are 24 months of age or younger at the beginning of RSV season,
- with hemodynamically significant congenital heart disease (CHD) and who are 24 months of age or younger at the beginning of RSV season [see Clinical Studies (14) ].

Limitations of Use:

The safety and efficacy of Synagis have not been established for treatment of RSV disease [see Warnings and Precautions (5.4)] .

2 DOSAGE AND ADMINISTRATION

2.1 Dosing Information

The recommended dose of Synagis is 15 mg per kg of body weight given monthly by intramuscular injection. The first dose of Synagis should be administered prior to commencement of the RSV season and the remaining doses should be administered monthly throughout the RSV season. Children who develop an RSV infection should continue to receive monthly doses throughout the RSV season. In the northern hemisphere, the RSV season typically commences in November and lasts through April, but it may begin earlier or persist later in certain communities.

Synagis serum levels are decreased after cardio-pulmonary bypass [see Clinical Pharmacology (12.3) ].Children undergoing cardio-pulmonary bypass should receive an additional dose of Synagis as soon as possible after the cardio-pulmonary bypass procedure (even if sooner than a month from the previous dose). Thereafter, doses should be administered monthly as scheduled.

The efficacy of Synagis at doses less than 15 mg per kg, or of dosing less frequently than monthly throughout the RSV season, has not been established.

2.2 Administration Instructions

- DO NOT DILUTE THE PRODUCT.
- DO NOT SHAKE OR VIGOROUSLY AGITATE THE VIAL.
- Parenteral drug products should be inspected visually for particulate matter and discoloration prior to administration. Do not use any vials exhibiting particulate matter or discoloration.
- Using aseptic techniques, attach a sterile needle to a sterile syringe. Remove the flip top from the Synagis vial and wipe the rubber stopper with a disinfectant (e.g., 70% isopropyl alcohol). Insert the needle into the vial and withdraw into the syringe an appropriate volume of solution. Administer immediately after drawing the dose into the syringe.
- Synagis should be administered in a dose of 15 mg per kg intramuscularly using aseptic technique, preferably in the anterolateral aspect of the thigh. The gluteal muscle should not be used routinely as an injection site because of the risk of damage to the sciatic nerve. The dose (volume of injection in mL) per month = patient weight (kg) x 15 mg per kg ÷ 100 mg per mL of Synagis. Injection volumes over 1 mL should be given as a divided dose.
- Synagis is supplied as a single-dose vial and does not contain preservatives. Do not re-enter the vial after withdrawal of drug; discard unused portion. Only administer one dose per vial.
- Use sterile disposable syringes and needles. To prevent the transmission of hepatitis viruses or other infectious agents from one person to another, DO NOT reuse syringes and needles.

3 DOSAGE FORMS AND STRENGTHS

Single-dose liquid solution vials: 50 mg per 0.5 mL and 100 mg per 1 mL.

4 CONTRAINDICATIONS

Synagis is contraindicated in children who have had a previous significant hypersensitivity reaction to Synagis [see Warnings and Precautions (5.1) ].

5 WARNINGS AND PRECAUTIONS

5.1 Hypersensitivity Reactions

Cases of anaphylaxis and anaphylactic shock, including fatal cases, have been reported following initial exposure or re-exposure to Synagis. Other acute hypersensitivity reactions, which may be severe, have also been reported on initial exposure or re-exposure to Synagis. Signs and symptoms may include urticaria, pruritus, angioedema, dyspnea, respiratory failure, cyanosis, hypotonia, hypotension, and unresponsiveness. The relationship between these reactions and the development of antibodies to Synagis is unknown. If a significant hypersensitivity reaction occurs with Synagis, its use should be permanently discontinued. If anaphylaxis or other significant hypersensitivity reaction occurs, administer appropriate medications (e.g., epinephrine) and provide supportive care as required. If a mild hypersensitivity reaction occurs, clinical judgment should be used regarding cautious readministration of Synagis.

5.2 Coagulation Disorders

Synagis is for intramuscular use only. As with any intramuscular injection, Synagis should be given with caution to children with thrombocytopenia or any coagulation disorder.

5.3 RSV Diagnostic Test Interference

Palivizumab may interfere with immunological-based RSV diagnostic tests such as some antigen detection-based assays. In addition, palivizumab inhibits virus replication in cell culture, and therefore may also interfere with viral culture assays. Palivizumab does not interfere with reverse transcriptase-polymerase chain reaction based assays. Assay interference could lead to false-negative RSV diagnostic test results. Therefore, diagnostic test results, when obtained, should be used in conjunction with clinical findings to guide medical decisions [see Microbiology (12.4) ].

5.4 Treatment of RSV Disease

The safety and efficacy of Synagis have not been established for treatment of RSV disease.

5.5 Proper Administration

The single-dose vial of Synagis does not contain a preservative. Administration of Synagis should occur immediately after dose withdrawal from the vial. The vial should not be re-entered. Discard any unused portion.

6 ADVERSE REACTIONS

The most serious adverse reactions occurring with Synagis are anaphylaxis and other acute hypersensitivity reactions [see Warnings and Precautions (5.1) ].

6.1 Clinical Studies Experience

Because clinical trials are conducted under widely varying conditions, adverse reaction rates observed in the clinical trials of a drug cannot be directly compared to rates in the clinical trials of another drug and may not reflect the rates observed in practice.

The data described below reflect exposure to Synagis (n=1639) compared with placebo (n=1143) in children 3 days to 24.1 months of age at high risk of RSV-related hospitalization in two clinical trials. Trial 1 was conducted during a single RSV season and studied a total of 1502 children less than or equal to 24 months of age with BPD or infants with premature birth (less than or equal to 35 weeks gestation) who were less than or equal to 6 months of age at study entry. Trial 2 was conducted over four consecutive seasons among a total of 1287 children less than or equal to 24 months of age with hemodynamically significant congenital heart disease.

In Trials 1 and 2 combined, fever and rash were each reported more frequently among Synagis than placebo recipients, 27% versus 25%, and 12% versus 10%, respectively. Adverse reactions observed in the 153-patient crossover study comparing the liquid and lyophilized formulations were comparable for the two formulations, and were similar to those observed with Synagis in Trials 1 and 2.

Immunogenicity

In Trial 1, the incidence of anti-palivizumab antibody following the fourth injection was 1.1% in the placebo group and 0.7% in the Synagis group. In children receiving Synagis for a second season, one of the fifty-six children had transient, low titer reactivity. This reactivity was not associated with adverse events or alteration in serum concentrations. Immunogenicity was not assessed in Trial 2.

A trial of high-risk preterm children less than or equal to 24 months of age was conducted to evaluate the immunogenicity of the lyophilized formulation of Synagis (used in Trials 1 and 2 above) and the liquid formulation of Synagis. Three hundred seventy-nine children contributed to the 4 to 6 months post-final dose analysis. The rate of anti-palivizumab antibodies at this time point was low in both formulation groups (anti-palivizumab antibodies were not detected in any subject in the liquid formulation group and were detected in one subject in the lyophilized group (0.5%), with an overall rate of 0.3% for both treatment groups combined).

These data reflect the percentage of children whose test results were considered positive for antibodies to palivizumab in an enzyme-linked immunosorbent assay (ELISA) and are highly dependent on the sensitivity and specificity of the assay.

The ELISA has substantial limitations in detecting anti-palivizumab antibodies in the presence of palivizumab. Immunogenicity samples tested with the ELISA assay likely contained palivizumab at levels that may interfere with the detection of anti-palivizumab antibodies.

An electrochemical luminescence (ECL) based immunogenicity assay, with a higher tolerance for palivizumab presence compared to the ELISA, was used to evaluate the presence of anti-palivizumab antibodies in subject samples from two additional clinical trials. The rates of anti-palivizumab antibody positive results in these trials were 1.1% and 1.5%.

6.2 Postmarketing Experience

The following adverse reactions have been identified during post approval use of Synagis. Because these reactions are reported voluntarily from a population of uncertain size, it is not always possible to reliably estimate their frequency or establish a causal relationship to drug exposure.

Blood and Lymphatic System Disorders:severe thrombocytopenia (platelet count less than 50,000 per microliter)

General Disorders and Administration Site Conditions:injection site reactions

Limited information from post-marketing reports suggests that, within a single RSV season, adverse events after a sixth or greater dose of Synagis are similar in character and frequency to those after the initial five doses.

7 DRUG INTERACTIONS

No formal drug-drug interaction studies were conducted. In Trial 1, the proportions of children in the placebo and Synagis groups who received routine childhood vaccines, influenza vaccine, bronchodilators, or corticosteroids were similar and no incremental increase in adverse reactions was observed among children receiving these agents.

8 USE IN SPECIFIC POPULATIONS

8.1 Pregnancy

Risk Summary

Synagis is not indicated for use in females of reproductive potential.

8.2 Lactation

Risk Summary

Synagis is not indicated for use in females of reproductive potential.

8.4 Pediatric Use

The safety and effectiveness of Synagis in children older than 24 months of age at the start of dosing have not been established [see Clinical Studies (14) ].

10 OVERDOSAGE

Overdoses with doses up to 85 mg per kg have been reported in clinical studies and post-marketing experience with Synagis, and in some cases, adverse reactions were reported. In case of overdosage, it is recommended that the patient be monitored for any signs or symptoms of adverse reactions and appropriate symptomatic treatment instituted.

11 DESCRIPTION

Palivizumab is a humanized monoclonal antibody (IgG1κ) produced by recombinant DNA technology, directed to an epitope in the A antigenic site of the F protein of RSV. Palivizumab is a composite of human (95%) and murine (5%) antibody sequences. The human heavy chain sequence was derived from the constant domains of human IgG1 and the variable framework regions of the VHgenes Cor and Cess. The human light chain sequence was derived from the constant domain of Cκ and the variable framework regions of the VLgene K104 with Jκ -4. The murine sequences were derived from a murine monoclonal antibody, Mab 1129, in a process that involved the grafting of the murine complementarity determining regions into the human antibody frameworks. Palivizumab is composed of two heavy chains and two light chains and has a molecular weight of approximately 148,000 Daltons.

Synagis is supplied as a sterile, preservative-free liquid solution at 100 mg per mL to be administered by intramuscular injection. Thimerosal or other mercury-containing salts are not used in the production of Synagis. The solution has a pH of 6.0 and should appear clear or slightly opalescent.

Each 100 mg single-dose vial of Synagis liquid solution contains 100 mg of palivizumab and also contains chloride (0.5 mg), glycine (0.1 mg), and histidine (3.9 mg), in a volume of 1 mL.

Each 50 mg single-dose vial of Synagis liquid solution contains 50 mg of palivizumab and also contains chloride (0.2 mg), glycine (0.06 mg), and histidine (1.9 mg), in a volume of 0.5 mL.

12 CLINICAL PHARMACOLOGY

12.1 Mechanism of Action

Palivizumab is a recombinant humanized monoclonal antibody with anti-RSV activity [see Microbiology (12.4) ].

12.3 Pharmacokinetics

In children less than or equal to 24 months of age without congenital heart disease (CHD), the mean half-life of palivizumab was 20 days and monthly intramuscular doses of 15 mg per kg achieved mean ± SD 30 day trough serum drug concentrations of 37 ± 21 mcg per mL after the first injection, 57 ± 41 mcg per mL after the second injection, 68 ± 51 mcg per mL after the third injection, and 72 ± 50 mcg per mL after the fourth injection. Trough concentrations following the first and fourth Synagis dose were similar in children with CHD and in non-cardiac patients. In children given Synagis for a second season, the mean ± SD serum concentrations following the first and fourth injections were 61 ± 17 mcg per mL and 86 ± 31 mcg per mL, respectively.

In 139 children less than or equal to 24 months of age with hemodynamically significant CHD who received Synagis and underwent cardio-pulmonary bypass for open-heart surgery, the mean ± SD serum palivizumab concentration was 98 ± 52 mcg per mL before bypass and declined to 41 ± 33 mcg per mL after bypass, a reduction of 58% [see Dosage and Administration (2.1) ].The clinical significance of this reduction is unknown.

Specific studies were not conducted to evaluate the effects of demographic parameters on palivizumab systemic exposure. However, no effects of gender, age, body weight, or race on palivizumab serum trough concentrations were observed in a clinical study with 639 children with CHD (less than or equal to 24 months of age) receiving five monthly intramuscular injections of 15 mg per kg of Synagis.

The pharmacokinetics and safety of Synagis liquid solution and Synagis lyophilized formulation administered via intramuscular injection at 15 mg per kg were studied in a cross-over trial of 153 infants less than or equal to 6 months of age with a history of prematurity. The results of this trial indicated that the trough serum concentrations of palivizumab were comparable between the liquid solution and the lyophilized formulation, which was the formulation used in the clinical studies.

A population pharmacokinetic analysis was performed across 22 studies in 1800 patients (1684 pediatric and 116 adult patients) to characterize palivizumab pharmacokinetics and inter-subject variability in serum concentrations. Palivizumab pharmacokinetics was described by a two-compartment linear model with an elimination half-life of 24.5 days in pediatric patients. Clearance of palivizumab in a typical pediatric patient (body weight 4.5 kg) less than or equal to 24 months of age without CHD was estimated to be 11 mL per day with a bioavailability of 70% following intramuscular administration. The inter-patient variability in drug clearance was 48.7% (CV%). Covariate analysis did not identify any factors that could account for the inter-patient variability in order to predict serum concentrations a priori in an individual patient.

12.4 Microbiology

Mechanism of Action

Palivizumab, a recombinant humanized monoclonal antibody which provides passive immunity against RSV, acts by binding the RSV envelope fusion protein (RSV F) on the surface of the virus and blocking a critical step in the membrane fusion process. Palivizumab also prevents cell-to-cell fusion of RSV-infected cells.

Antiviral Activity

The antiviral activity of palivizumab was assessed in a microneutralization assay in which increasing concentrations of antibody were incubated with RSV prior to addition of the human epithelial cells HEp-2. After incubation for 4-5 days, RSV antigen was measured in an ELISA assay. The neutralization titer (50% effective concentration [EC50]) is expressed as the antibody concentration required to reduce detection of RSV antigen by 50% compared with untreated virus-infected cells. Palivizumab exhibited median EC50values of 0.65 mcg per mL (mean 0.75 ± 0.53 mcg per mL; n=69, range 0.07-2.89 mcg per mL) and 0.28 mcg per mL (mean 0.35 ± 0.23 mcg per mL; n=35, range 0.03-0.88 mcg per mL) against clinical RSV A and RSV B isolates, respectively. The majority of clinical RSV isolates tested (n=96) were collected from subjects across the United States (CA, CO, CT, IL, MA, NC, NY, PA, RI, TN, TX, VA), with the remainder from Japan (n=1), Australia (n=5) and Israel (n=2). These isolates encoded the most common RSV F sequence polymorphisms found among clinical isolates worldwide.

Palivizumab serum concentrations of greater than or equal to 40 mcg per mL have been shown to reduce pulmonary RSV replication in the cotton rat model of RSV infection by 100-fold.

Resistance

Palivizumab binds a highly conserved region on the extracellular domain of mature RSV F, referred to as antigenic site II or site A, which encompasses amino acids 262 to 275. All RSV mutants that exhibit resistance to palivizumab have been shown to contain amino acid changes in this region on the F protein.

F protein sequence variations within antigenic site A: Amino acid substitutions in antigenic site A selected either in cell culture, in animal models, or in human subjects that resulted in palivizumab resistance were N262D, N268I, K272E/M/N/Q/T, and S275F/L. RSV variants expressing the K272N substitution in F protein showed a 5164 ± 1731-fold decrease in susceptibility (i.e., fold increase in EC50value) when compared to the wild-type RSV, while variants containing the N262D, S275F/L, or K272E/M/Q/T substitutions showed a greater than 25,000-fold decrease in susceptibility to palivizumab. The N268I substitution conferred partial resistance to palivizumab; however, fold changes in susceptibility were not quantified for this mutant. Studies carried out to investigate the mechanism of virus escape from palivizumab showed a correlation between antibody binding and virus neutralization. RSV with substitutions in antigenic site A that were resistant to neutralization by palivizumab did not bind to palivizumab.

At least one of the palivizumab resistance-associated substitutions, N262D, K272E/Q, or S275F/L was identified in 8 of 126 clinical RSV (59 RSV A and 67 RSV B) isolates from subjects who failed immunoprophylaxis, resulting in a combined resistance-associated mutation frequency of 6.3%. A review of clinical findings revealed no association between antigenic A site sequence changes and RSV disease severity among children receiving palivizumab immunoprophylaxis who develop RSV lower respiratory tract disease.

Analysis of 254 clinical RSV isolates (145 RSV A and 109 RSV B) collected from immunoprophylaxis-naïve subjects revealed palivizumab resistance-associated substitutions in 2 (1 with N262D and 1 with S275F), resulting in a resistance-associated mutation frequency of 0.79%.

F protein sequence variations outside antigenic site A: In addition to the sequence variations in antigenic site A known to confer palivizumab resistance, F protein substitutions T100A, G139S, N165D/V406I; T326A, V450A in RSV A, and T74I, A147V, I206L, S285G, V450I, T455I in RSV B were identified in viruses isolated from failures of immunoprophylaxis. These substitutions were not identified in RSV F sequences derived from 254 clinical isolates from immunoprophylaxis-naïve subjects and thus are considered treatment-associated and non-polymorphic. Recombinant RSV B encoding the S285G substitution exhibited palivizumab sensitivity (EC50value = 0.39 ± 0.02 mcg per mL) similar to recombinant wild-type RSV B (EC50value = 0.17 ± 0.02 mcg per mL).

Palivizumab susceptibility of RSV encoding common F protein sequence polymorphisms located proximal to antigenic site A was evaluated. Recombinant RSV A encoding N276S (EC50value = 0.72 ± 0.07 mcg per mL), and recombinant RSV B with S276N (EC50value = 0.42 ± 0.04 mcg per mL), exhibited sensitivities comparable to the corresponding recombinant wild-type RSV A (EC50value = 0.63 ± 0.22 mcg per mL) and RSV B (EC50value = 0.23 ± 0.07 mcg per mL). Likewise, RSV B clinical isolates containing the polymorphic variation V278A were at least as sensitive to neutralization by palivizumab (EC50range 0.08-0.45 mcg per mL) as laboratory strains of wild-type RSV B (EC50value = 0.54 ± 0.08 mcg per mL). No known polymorphic or non-polymorphic sequence variations outside the antigenic site A on RSV F have been demonstrated to render RSV resistant to neutralization by palivizumab.

Interference of RSV Diagnostic Assays by Palivizumab

Interference with immunologically-based RSV diagnostic assays by palivizumab has been observed in laboratory studies. Rapid chromatographic/enzyme immunoassays (CIA/EIA), immunofluorescence assays (IFA), and direct immunofluorescence assays (DFA) using monoclonal antibodies targeting RSV F protein may be inhibited. Therefore, caution should be used in interpreting negative immunological assay results when clinical observations are consistent with RSV infection. A reverse transcriptase-polymerase chain reaction (RT-PCR) assay, which is not inhibited by palivizumab, may prove useful for laboratory confirmation of RSV infection [see Warnings and Precautions (5.3) ].

13 NONCLINICAL TOXICOLOGY

13.1 Carcinogenesis, Mutagenesis, Impairment of Fertility

Carcinogenesis, mutagenesis, and reproductive toxicity studies have not been performed.

14 CLINICAL STUDIES

The safety and efficacy of Synagis were assessed in two randomized, double-blind, placebo-controlled trials of prophylaxis against RSV infection in children at high risk of an RSV-related hospitalization. Trial 1 was conducted during a single RSV season and studied a total of 1502 children less than or equal to 24 months of age with BPD or infants with premature birth (less than or equal to 35 weeks gestation) who were less than or equal to 6 months of age at study entry. Trial 2 was conducted over four consecutive seasons among a total of 1287 children less than or equal to 24 months of age with hemodynamically significant congenital heart disease. In both trials participants received 15 mg per kg Synagis or an equivalent volume of placebo via intramuscular injection monthly for five injections and were followed for 150 days from randomization. In Trial 1, 99% of all subjects completed the study and 93% completed all five injections. In Trial 2, 96% of all subjects completed the study and 92% completed all five injections. The incidence of RSV hospitalization is shown in Table 1. The results were shown to be statistically significant using Fisher's exact test.

Table 1: Incidence of RSV Hospitalization by Treatment Group
Trial |  | Placebo | Synagis | Difference Between Groups | Relative Reduction
Trial 1 Impact-RSV | N | 500 | 1002
Trial 1 Impact-RSV | Hospitalization | 53 (10.6%) | 48 (4.8%) | 5.8% | 55%
Trial 2 CHD | N | 648 | 639
Trial 2 CHD | Hospitalization | 63 (9.7%) | 34 (5.3%) | 4.4% | 45%

In Trial 1, the reduction of RSV hospitalization was observed both in children with BPD (34/266 [12.8%] placebo versus 39/496 [7.9%] Synagis) and in premature infants without BPD (19/234 [8.1%] placebo versus 9/506 [1.8%] Synagis). In Trial 2, reductions were observed in acyanotic (36/305 [11.8%] placebo versus 15/300 [5.0%] Synagis) and cyanotic children (27/343 [7.9%] placebo versus 19/339 [5.6%] Synagis).

The clinical studies do not suggest that RSV infection was less severe among children hospitalized with RSV infection who received Synagis for RSV prophylaxis compared to those who received placebo.

16 HOW SUPPLIED/STORAGE AND HANDLING

Synagis is supplied in single-dose vials as a preservative-free, sterile liquid solution at 100 mg per mL for intramuscular injection.

50 mg vial NDC 66658-230-01

The 50 mg vial contains 50 mg Synagis in 0.5 mL.

100 mg vial NDC 66658-231-01

The 100 mg vial contains 100 mg Synagis in 1 mL.

The rubber stopper used for sealing vials of Synagis is not made with natural rubber latex.

Storage

Upon receipt and until use, Synagis should be stored between 2°C and 8°C (36°F and 46°F) in its original container. DO NOT freeze. DO NOT use beyond the expiration date.

17 PATIENT COUNSELING INFORMATION

Advise the patient's caregiver to read the FDA-approved patient labeling (Patient Information)

Hypersensitivity Reactions

Inform the patient's caregiver of the signs and symptoms of potential hypersensitivity reactions, and advise the caregiver to seek medical attention immediately if the child experiences a severe hypersensitivity reaction to Synagis [see Contraindications (4) and Warnings and Precautions (5.1) ].

Administration

Advise the patient's caregiver that Synagis should be administered by a healthcare provider once a month during the RSV season by intramuscular injection and the importance of compliance with the full course of therapy [see Dosage and Administration (2)] .

Synagis® is a registered trademark of Arexis AB c/o Swedish Orphan Biovitrum AB (publ).

sobi

Manufactured by:
Swedish Orphan Biovitrum AB (publ)
Stockholm, Sweden

Distributed by:
Sobi Inc.
77 4th Avenue, 3rd FloorWaltham, MA 02451-7559

U.S License No. 1859
Issued: 11/2020

PATIENT INFORMATION
SYNAGIS® (Si-na-jis)
(palivizumab)
injection

What is SYNAGIS?
SYNAGIS is a prescription medication that is used to help prevent a serious lung disease caused by Respiratory Syncytial Virus (RSV) in children:

- born prematurely (at or before 35 weeks) andwho are 6 months of age or less at the beginning of RSV season,
- who have a chronic lung condition called bronchopulmonary dysplasia (BPD), that needed medical treatment within the last 6 months, andwho are 24 months of age or less at the beginning of RSV season,
- born with certain types of heart disease andwho are 24 months of age or less at the beginning of RSV season.

SYNAGIS contains man-made, disease-fighting proteins called antibodies.
It is not known if SYNAGIS is safe and effective to treat the symptoms of RSV in a child who already has RSV. Synagis is used to help prevent RSV disease.
It is not known if SYNAGIS is safe and effective in children who are older than 24 months of age at the start of dosing.

Who should not receive SYNAGIS?
Your child should not receive SYNAGIS if they have ever had a severe allergic reaction to it. See the end of this leaflet for a complete list of ingredients in SYNAGIS. Signs and symptoms of a severe allergic reaction could include:

- severe rash, hives, or itching skin
- swelling of the lips, tongue, or face
- swelling of the throat, difficulty swallowing
- difficult, rapid, or irregular breathing

- bluish color of skin, lips, or under fingernails
- muscle weakness or floppiness
- unresponsiveness

Before your child receives SYNAGIS, tell your healthcare provider about all of your child's medical conditions, including if your child:

- has ever had a reaction to SYNAGIS.
- has bleeding or bruising problems. SYNAGIS is given by injection. If your child has a problem with bleeding or bruises easily, an injection could cause a problem.

Tell your child's healthcare provider about all the medicines your child takes, including prescription and over-the-counter medicines, vitamins, and herbal supplements.

How is SYNAGIS given?

- SYNAGIS is given as a monthly injection, usually in the thigh (leg) muscle, by your child's healthcare provider.
- Your child's healthcare provider will give you detailed instructions on when SYNAGIS will be given.
  - “RSV season” is the time of year when RSV infections most commonly happen, usually fall through spring, but it may begin earlier or last longer in certain areas. During this time, when RSV is most active, your child will need to receive SYNAGIS injections. Your healthcare provider can tell you when the RSV season starts in your area.
  - Your child should receive the first SYNAGIS injection before the RSV season startsto help prevent RSV infection. If the season has already started, your child should receive their first SYNAGIS injection as soon as possible to help protect them when exposure to the virus is more likely.
  - SYNAGIS is needed every 28-30 days during the RSV season. Each injection of SYNAGIS helps protect your child from severe RSV disease for about 1 month. Keep all of your child's appointments with your healthcare provider.
- If your child misses an injection, talk to your healthcare provider and schedule another injection as soon as possible.
- Your child may still get severe RSV disease after receiving SYNAGIS.Talk to your healthcare provider about what symptoms to look for. If your child gets a RSV infection, they should continue to receive their scheduled SYNAGIS injections to help prevent severe disease from new RSV infections.
- If your child has certain types of heart disease and has corrective surgery, your healthcare provider may need to give your child an additional SYNAGIS injection soon after surgery.

What are the possible side effects of SYNAGIS?
SYNAGIS may cause serious side effects including:

- Severe allergic reactions.Severe allergic reactions may happen after any injectionof SYNAGIS, and may be life-threatening or cause death. Call your healthcare provider or get medical help right away if your child has any of the signs or symptoms of a serious allergic reaction. See “ Who should not receive SYNAGIS?” .

The most common side effects of SYNAGIS include fever and rash.
These are not all the possible side effects of SYNAGIS.
Call your doctor for medical advice about side effects. You may report side effects to FDA at 1-800-FDA-1088.
You may also report side effects at 1866-773-5274.

General information about the safe and effective use of SYNAGIS.
Medicines are sometimes prescribed for purposes other than those listed in Patient Information leaflets.
You can ask your pharmacist or healthcare provider for information about SYNAGIS that is written for health professionals.

What are the ingredients in SYNAGIS?
Active ingredient: palivizumab
Inactive ingredients: chloride, glycine, and histidine

Manufactured by: Swedish Orphan Biovitrum AB (publ) , Stockholm, Sweden
Synagis® is a registered trademark of Arexis AB c/o Swedish Orphan Biovitrum AB (publ).

sobi

For more information, go to www.synagis.com or call 1866-773-5274.

This Patient Information has been approved by the U.S. Food and Drug Administration

Revised: 11/2021

Principal Display Panel - 50 mg/0.5 mL Carton Label

NDC 66658-230-01

SYNAGIS®

PALIVIZUMAB

50 mg/0.5 mL

For Intramuscular Injection Only

Store at 2 to 8°C (36 to 46°F).

Single-dose vial.

Discard unused portion.

Principal Display Panel - 50 mg/0.5 mL Vial Label

NDC 66658-230-01

50 mg/0.5 mL

SYNAGIS®

PALIVIZUMAB

For Intramuscular
Injection Only

US Lic. 1859

Principal Display Panel - 100 mg/mL Carton Label

NDC 66658-231-01

SYNAGIS®

PALIVIZUMAB

100 mg/mL

For Intramuscular Injection Only

Store at 2 to 8°C (36 to 46°F).

Single-dose vial.

Discard unused portion.

Principal Display Panel - 100 mg/mL Vial Label

NDC 66658-231-01

100 mg/mL

SYNAGIS®

PALIVIZUMAB

For Intramuscular
Injection Only

US Lic. 1859